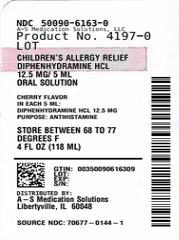 DRUG LABEL: children allergy relief dye free cherry
NDC: 50090-6163 | Form: SOLUTION
Manufacturer: A-S Medication Solutions
Category: otc | Type: Human OTC Drug Label
Date: 20231101

ACTIVE INGREDIENTS: DIPHENHYDRAMINE HYDROCHLORIDE 12.5 mg/5 mL
INACTIVE INGREDIENTS: CARBOXYMETHYLCELLULOSE SODIUM, UNSPECIFIED FORM; ANHYDROUS CITRIC ACID; glycerin; water; sodium benzoate; sorbitol; SACCHARIN SODIUM ANHYDROUS

SunMark Children Allergy Relief Dye Free Cherry

ACTIVE INGREDIENT(in each 5 mL)

Diphenhydramine HCl 12.5 mg

PURPOSE

Antihistamine

USES

- temporarily relieves these symptoms due to hay fever or other upper respiratory allergies:

- runny nose
- itchy, watery eyes
- sneezing
- itching of the nose or throat

WARNINGS

.

DO NOT USE

- to make a child sleepy
- with any other product containing diphenhydramine, even one used on skin

ASK A DOCTOR BEFORE USE IF THE CHILD HAS

- glaucoma
- a breathing problem such as chronic bronchitis

ASK A DOCTOR OR PHARMACIST BEFORE USE IF THE CHILD IS

taking sedatives or tranquilizers

WHEN USING THIS PRODUCT

- sedatives and tranquilizers may increase drowsiness
- marked drowsiness may occur
- excitability may occur, especially in children

KEEP OUT OF REACH OF CHILDREN

In case of overdose, get medical help or contact a poison control center right away

(1-800-222-1222).

DIRECTIONS

- find right dose on chart below

- mL=milliliter
- measure only with dosing cup provided
- do not use dosing cup with other products
- take every 4 to 6 hours, or as directed by a doctor
- do not take more than 6 doses in 24 hours

AGE(yr) | DOSE(mL)
children under 2 years | do not use
children 2 to 5 years | do not use unless directed by a doctor
children 6 to 11 years | 5 mL to 10 mL

OTHER INFORMATION

- each 5 mL contains: sodium 5 mg
- dosing cup provided
- store between 20 - 25oC (68o- 77oF)

INACTIVE INGREDIENTS

carboxymethylcellulose sodium, citric acid, flavors, glycerin, purified water, saccharin sodium, sodium benzoate, sorbitol.

QUESTIONS OR COMMENTS?

Call 833-358-6431 Monday to Friday 9:00 am to 7:00 pm EST

HOW SUPPLIED

Product: 50090-6163

NDC: 50090-6163-0 118 mL in a BOTTLE / 1 in a CARTON